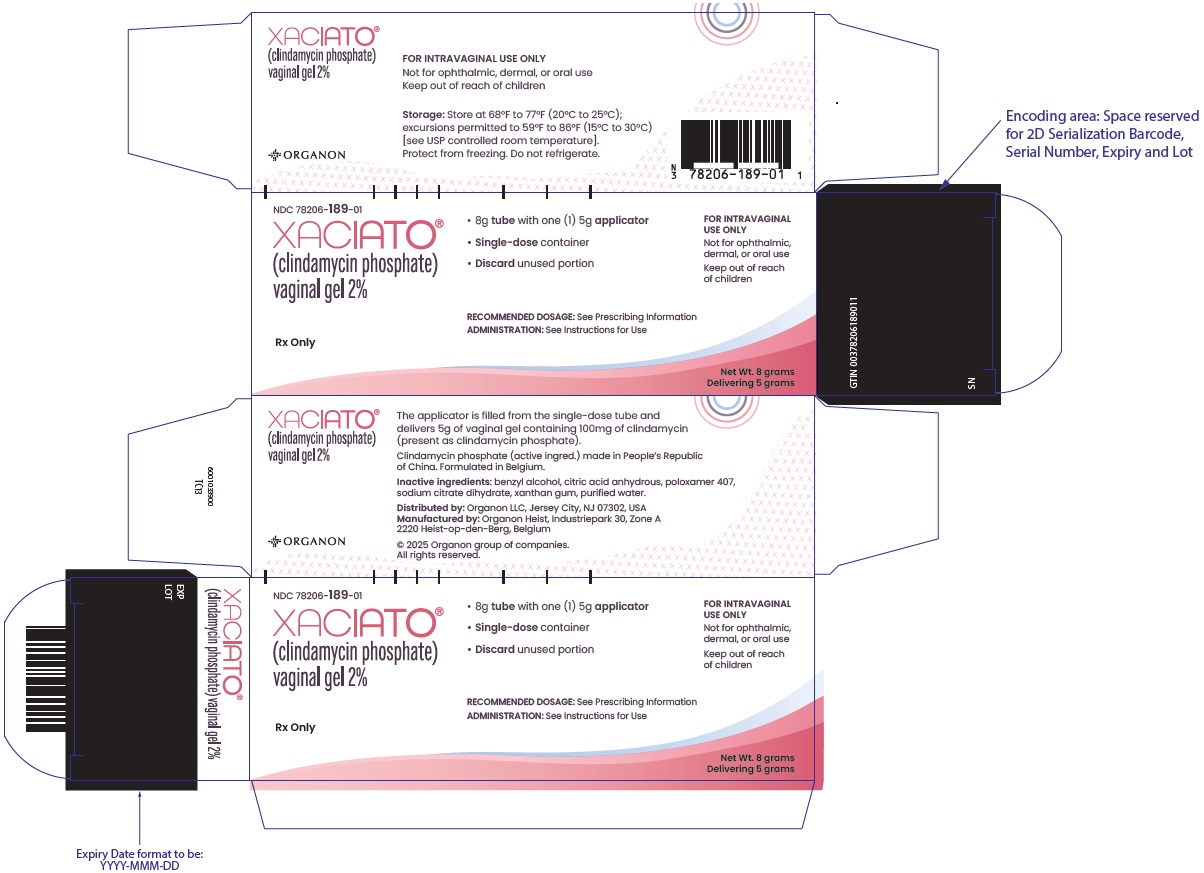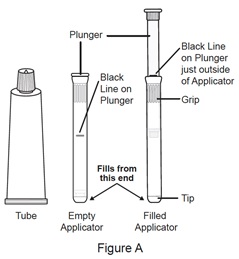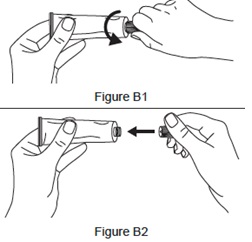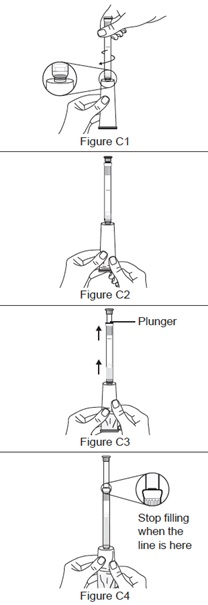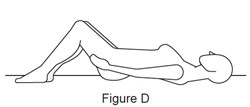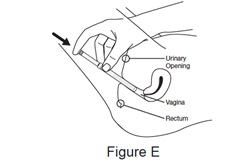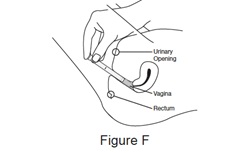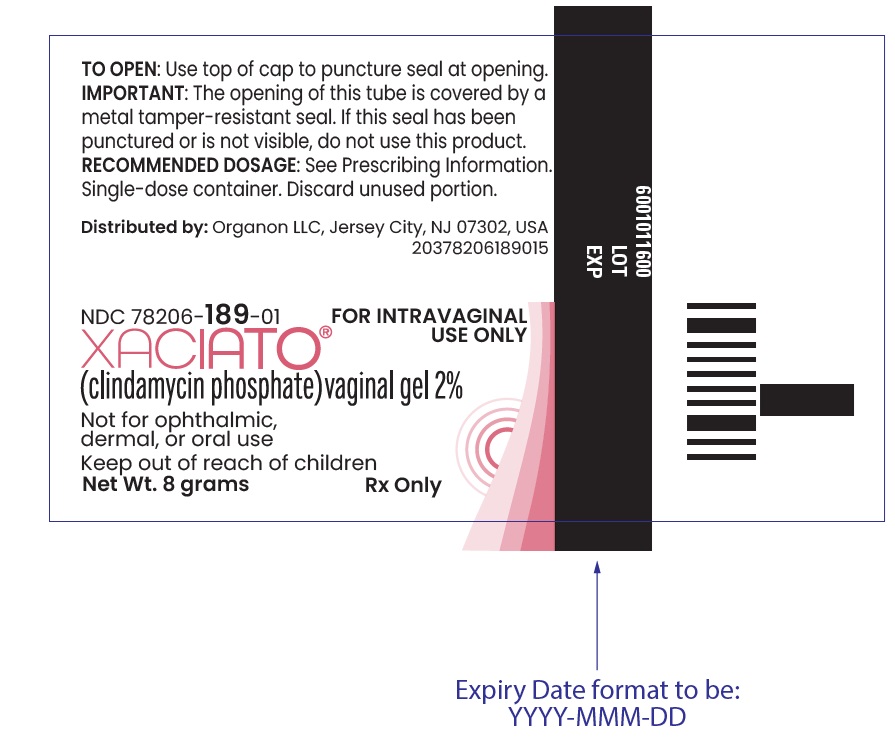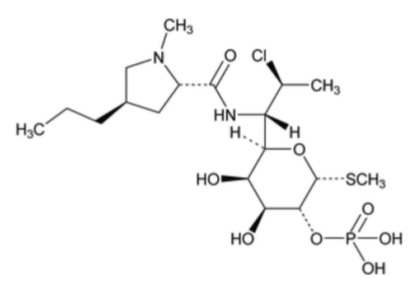 DRUG LABEL: XACIATO
NDC: 78206-189 | Form: GEL
Manufacturer: Organon LLC
Category: prescription | Type: HUMAN PRESCRIPTION DRUG LABEL
Date: 20260219

ACTIVE INGREDIENTS: Clindamycin phosphate 100 mg/5 g
INACTIVE INGREDIENTS: BENZYL ALCOHOL; CITRIC ACID MONOHYDRATE; POLOXAMER 407; WATER; TRISODIUM CITRATE DIHYDRATE; XANTHAN GUM

HIGHLIGHTS OF PRESCRIBING INFORMATION

These highlights do not include all the information needed to use XACIATO safely and effectively. See full prescribing information for XACIATO
XACIATO® (clindamycin phosphate) vaginal gel
Initial U.S. Approval: 2021

1 INDICATIONS AND USAGE

XACIATO is a lincosamide antibacterial indicated for the treatment of bacterial vaginosis in female patients 12 years of age and older. (1.1)

2 DOSAGE AND ADMINISTRATION

- Administer one applicatorful (5 g of gel containing 100 mg of clindamycin) once intravaginally as a single dose at any time of the day. (2)
- Not for ophthalmic, dermal, or oral use. (2)

3 DOSAGE FORMS AND STRENGTHS

Vaginal gel: 2% clindamycin present as clindamycin phosphate in an 8 g tube. One single-dose, user-filled disposable applicator delivers 5 g of gel containing 100 mg of clindamycin. (3)

4 CONTRAINDICATIONS

History of hypersensitivity to clindamycin or lincomycin. (4.1)

5 WARNINGS AND PRECAUTIONS

- Clostridioides difficile-Associated Diarrhea: Discontinue and evaluate if diarrhea occurs. (5.1)
- Use with Polyurethane Condoms: Polyurethane condoms are not recommended during treatment with XACIATO or for 7 days following treatment. During this time period, polyurethane condoms may not be reliable for preventing pregnancy or for protecting against transmission of HIV and other sexually transmitted diseases. Latex or polyisoprene condoms should be used (5.2)

6 ADVERSE REACTIONS

The most common adverse reactions reported in >2% of patients and at a higher rate in the XACIATO group than in the placebo group were vulvovaginal candidiasis and vulvovaginal discomfort. (6.1)

To report SUSPECTED ADVERSE REACTIONS, contact Organon LLC, at 1-844-674-3200 or FDA at 1-800-FDA-1088 or www.fda.gov/medwatch.

FULL PRESCRIBING INFORMATION

1 INDICATIONS AND USAGE

1.1 Bacterial Vaginosis

XACIATO® is indicated for the treatment of bacterial vaginosis in females 12 years and older [see Use in Specific Populations (8.1) and Clinical Studies (14)].

2 DOSAGE AND ADMINISTRATION

The recommended dosage of XACIATO is one applicatorful (5 g of vaginal gel containing 100 mg of clindamycin) administered once intravaginally as a single dose at any time of the day [see Clinical Studies (14)]. Place the used tube with any remaining gel and used applicator in the container box and deposit in a trash container after use [see Instructions for Use].

XACIATO is not for ophthalmic, dermal, or oral use.

3 DOSAGE FORMS AND STRENGTHS

Vaginal gel: 2% clindamycin (present as clindamycin phosphate) as a clear, colorless, viscous gel in an 8 g tube. One user-filled single-dose disposable applicator delivers 5 g of gel containing 100 mg of clindamycin.

4 CONTRAINDICATIONS

4.1 Hypersensitivity

XACIATO is contraindicated in individuals with a history of hypersensitivity to clindamycin or lincomycin. [see Adverse Reactions (6.2)].

5 WARNINGS AND PRECAUTIONS

5.1 Clostridioides difficile-Associated Diarrhea (CDAD)

Clostridioides difficile-associated diarrhea (CDAD) has been reported with use of nearly all antibacterial agents, including clindamycin, and may range in severity from mild diarrhea to fatal colitis. Treatment with antibacterial agents alters the normal flora of the colon which can lead to overgrowth of C. difficile.

C. difficile produces toxins A and B which contribute to the development of CDAD. Hypertoxin producing strains of C. difficile cause increased morbidity and mortality, as these infections can be refractory to antimicrobial therapy and may require colectomy. CDAD must be considered in all patients who present with diarrhea following antibacterial use. Careful medical history is necessary since CDAD has been reported to occur over two months after the administration of antibacterial agents. Patients with inflammatory bowel disease, including ulcerative colitis and Crohn’s disease, have a higher risk of developing CDAD.

If CDAD is suspected or confirmed, ongoing antibacterial use not directed against C. difficile may need to be discontinued. Appropriate fluid and electrolyte management, protein supplementation, antibacterial treatment of C. difficile, and surgical evaluation should be instituted as clinically indicated [see Adverse Reactions (6.2)].

5.2 Use with Polyurethane Condoms

XACIATO is not compatible with and may weaken polyurethane condoms; therefore, their use is not recommended during treatment with XACIATO or for 7 days following treatment. During this time period, polyurethane condoms may not be reliable for preventing pregnancy or for protecting against transmission of HIV and other sexually transmitted diseases. Latex or polyisoprene condoms should be used [see Use in Specific Populations (8.3)].

5.3 Vaginal Candida Infections

XACIATO may result in the overgrowth of Candida spp. in the vagina resulting in vulvovaginal candidiasis which may require antifungal treatment [see Adverse Reactions (6.1)].

6 ADVERSE REACTIONS

The following clinically significant adverse reactions are described elsewhere in the labeling:

- Clostridioides difficile-Associated Diarrhea (CDAD) [see Warnings and Precautions (5.1)]
- Use with Polyurethane Condoms [see Warnings and Precautions (5.2)]
- Vaginal Candida Infections [see Warnings and Precautions (5.3)]

6.1 Clinical Trials Experience

Because clinical trials are conducted under widely varying conditions, adverse reaction rates observed in the clinical trials of a drug cannot be directly compared to rates in the clinical trials of another drug and may not reflect the rates observed in practice.

In the placebo-controlled trial (Trial 1), 202 patients with bacterial vaginosis were treated with a single dose of XACIATO, and 103 patients were treated with a single dose of placebo gel. The median age of the patients in the trial was 35 years (range 15-59 years). The population was 56% Black or African American and 41% White. Persons of Hispanic or Latino ethnicity made up 25% of the population. A history of prior bacterial vaginosis was noted in 89% of the population.

Most Common Adverse Reactions

Adverse reactions were reported by 76/202 (38%) of patients who received XACIATO and 28/103 (27%) of patients who received placebo in Trial 1. Table 1 displays the most common adverse reactions (occurring in >2% of patients and at a higher rate in the XACIATO group than in the placebo group) in Trial 1.

Table 1: Adverse Reactions Occurring in >2% of Patients Receiving XACIATO in Trial 1
Adverse Reaction | XACIATO; N=202; n (%) | Placebo; N=103; n (%)
Vulvovaginal candidiasis | 35 (17) | 4 (4)
Vulvovaginal discomfort [Vulvovaginal discomfort includes the terms vulvovaginal pruritus, vulvovaginal burning sensation, vulvovaginal erythema, vulvovaginal dryness, and vulvovaginal discomfort.] | 13 (6) | 5 (5)

6.2 Other Clindamycin Formulations

XACIATO affords low peak serum levels and systemic exposure of clindamycin compared to an oral or intravenous dose of clindamycin [see Clinical Pharmacology (12.3)]. Data from well-controlled trials directly comparing clindamycin administered orally to clindamycin administered vaginally are not available.

The following additional adverse reactions and altered laboratory tests have been reported with the oral or parenteral use of clindamycin:

Gastrointestinal: Abdominal pain, esophagitis, nausea, Clostridioides difficile-associated diarrhea [see Warnings and Precautions (5.1)].

Hematopoietic: Transient neutropenia (leukopenia), eosinophilia, agranulocytosis, and thrombocytopenia have been reported. No direct etiologic relationship to concurrent clindamycin therapy could be made in any of these reports.

Hypersensitivity Reactions: Maculopapular rash, vesiculobullous rash, and urticaria have been observed during drug therapy. Generalized mild to moderate morbilliform-like skin rashes are the most frequently reported of all adverse reactions. Cases of erythema multiforme, some resembling Stevens-Johnson syndrome, have been associated with clindamycin. A few cases of anaphylactoid reactions have been reported.

Liver: Jaundice and abnormalities in liver function tests have been observed during clindamycin therapy.

Musculoskeletal: Cases of polyarthritis have been reported.

Renal: Acute kidney injury.

Immune: Drug reaction with eosinophilia with systemic symptoms (DRESS) cases have been reported.

7 DRUG INTERACTIONS

7.1 Neuromuscular Blocking Agents

Systemic clindamycin has neuromuscular blocking properties that may enhance the action of other neuromuscular blocking agents. Therefore, it should be used with caution in patients receiving such agents.

8 USE IN SPECIFIC POPULATIONS

8.1 Pregnancy

Risk Summary

Other clindamycin vaginal products have been used to treat pregnant women during the second and third trimester. XACIATO has not been studied in pregnant women. However, based on the low systemic absorption of XACIATO following the intravaginal route of administration in nonpregnant women, maternal use is not likely to result in significant fetal exposure to the drug [see Clinical Pharmacology (12.3)]. Available data from published observational studies, based on first trimester exposure to oral and IV clindamycin, did not identify consistent increases in the rate of major birth defects. Available data from published observational studies and randomized controlled trials, based on second and third trimester exposure to oral and IV clindamycin, did not identify an increased risk of miscarriage or other adverse maternal or fetal outcomes. Most of the reported exposures to clindamycin occurred during the second and third trimesters of the pregnancy.

In animal reproduction studies, no adverse developmental outcomes were observed when XACIATO was vaginally administered to pregnant rats and rabbits during organogenesis at doses approximately equivalent to the recommended human dose. No evidence of any adverse developmental outcomes was observed when oral or subcutaneous doses of clindamycin were administered to pregnant rats and mice during organogenesis at doses 9 to 58 times the recommended human dose based on body surface area comparison (see Data).

The estimated background risk of major birth defects and miscarriage for the indicated population is unknown. All pregnancies have a background risk of birth defect, loss, or other adverse outcomes. In the U.S. general population, the estimated background risk of major birth defects and miscarriage in clinically recognized pregnancies is 2% to 4% and 15% to 20%, respectively.

Data

Animal Data
Reproduction studies performed during organogenesis in pregnant rats (gestational days 6-17) and rabbits (gestational days 7-19) administered vaginal XACIATO at 0.1 g and 1 g/day (2 mg and 20 mg clindamycin phosphate/day) showed no evidence of developmental toxicity. These doses are approximately equivalent to the applied recommended clinical dose based on g/cm^2 vaginal surface area and body surface area (BSA) comparisons.

Reproduction studies performed during organogenesis (gestational days 6-15) in pregnant rats and mice that were administered oral doses of clindamycin up to 600 mg/kg/day (58 and 29 times, respectively, the recommended human dose based on a body surface area comparison) or subcutaneous doses of clindamycin up to 250 mg/kg/day (24- and 12-times, respectively, the MRHD based on BSA comparisons) revealed no evidence of teratogenicity.

Vaginal administration of XACIATO to pregnant/lactating female rats during a pre- and post-natal development (gestation day 6 through gestation day 21) study at 2 mg clindamycin phosphate/day had no adverse effects on dams or their offspring.

8.2 Lactation

Risk Summary

Systemic absorption following intravaginal administration of clindamycin is low; therefore, transfer of clindamycin into breastmilk is likely to be low and adverse effects on the breastfed infant are not expected [see Clinical Pharmacology (12.3)]. There are no data on the effect of clindamycin on milk production.

The developmental and health benefits of breastfeeding should be considered along with the mother's clinical need for clindamycin and any potential adverse effects on the breastfed child from clindamycin or from the underlying maternal condition.

8.3 Males and Females of Reproductive Potential

Contraception

XACIATO is not compatible with and may weaken polyurethane condoms; therefore, use of polyurethane condoms is not recommended during and for 7 days following treatment with XACIATO. Advise patients to use latex or polyisoprene condoms for contraception during and for 7 days following treatment with XACIATO [see Warnings and Precautions (5.2)].

8.4 Pediatric Use

The safety and effectiveness of XACIATO have been established in females aged 12 years and older for the treatment of bacterial vaginosis. Use of XACIATO for this indication is supported by the extrapolation of clinical trial data from adequate and well controlled clinical studies in adult women. The safety and effectiveness of XACIATO have not been established in pediatric patients younger than 12 years of age for the treatment of bacterial vaginosis.

8.5 Geriatric Use

Clinical studies with XACIATO did not include any subjects 65 years of age or older to determine whether they respond differently than younger subjects.

11 DESCRIPTION

XACIATO vaginal gel contains clindamycin phosphate, a lincosamide antibacterial. The chemical name for clindamycin phosphate is methyl 7-chloro- 6,7,8-trideoxy-6-(1-methyl- trans-4-propyl-L-2-pyrrolidinecarboxamido)-1-thio-L- threo-(alpha)-D-galacto- octopyranoside 2-(dihydrogenphosphate). It has a molecular weight of 504.95, and the molecular formula is C18H34ClN2O8PS. The structural formula is represented below:

XACIATO is a clear, colorless, viscous gel, which contains clindamycin at a concentration of 2%. A single-dose user-filled disposable applicator delivers 5 g of vaginal gel containing 100 mg of clindamycin (present as 119 mg of clindamycin phosphate). The gel also contains benzyl alcohol, citric acid monohydrate or citric acid anhydrous, poloxamer 407, purified water, sodium citrate dihydrate, and xanthan gum.

12 CLINICAL PHARMACOLOGY

12.1 Mechanism of Action

Clindamycin is an antibacterial drug [see Microbiology (12.4)].

12.3 Pharmacokinetics

Clindamycin phosphate is a water-soluble ester prodrug of clindamycin. Biologically inactive clindamycin phosphate is converted to active clindamycin. Following a single intravaginal dose of 100 mg of XACIATO administered to 21 healthy female subjects, the arithmetic mean (range) peak plasma concentration was 69.2 ng/mL (3.8 to 236 ng/mL). The median (range) tmax occurred at 6 hours (4 to 96 hours). The mean Cmax of clindamycin for XACIATO was approximately 0.5% of that observed after the IV infusion of Clindamycin Phosphate in 0.9% Sodium Chloride, 900 mg clindamycin, every 8 hours.

12.4 Microbiology

Mechanism of Action

Clindamycin inhibits bacterial protein synthesis by binding to the 23S RNA of the 50S subunit of the ribosome. Clindamycin is predominantly bacteriostatic. Although clindamycin phosphate is inactive in vitro, rapid in vivo hydrolysis converts it to active clindamycin.

Resistance

Resistance to clindamycin is most often caused by modification of the target site on the ribosome, usually by chemical modification of RNA bases by point mutations in RNA or occasionally in proteins. Cross resistance has been demonstrated between lincosamides, macrolides and streptogramins B in some organisms. Cross resistance has been demonstrated between clindamycin and lincomycin.

Antibacterial Activity

Culture and sensitivity testing of bacteria are not routinely performed to establish the diagnosis of bacterial vaginosis [see Clinical Studies (14)]. Standard methodology for the susceptibility testing of the potential bacterial pathogens, Gardnerella vaginalis, Mobiluncus spp., or Mycoplasma hominis, has not been defined.

The following in vitro data are available, but their clinical significance is unknown. Clindamycin is active in vitro against most isolates of the following organisms reported to be associated with bacterial vaginosis:

Bacteroides spp.

Gardnerella vaginalis

Mobiluncus spp.

Mycoplasma hominis

Peptostreptococcus spp.

13 NONCLINICAL TOXICOLOGY

13.1 Carcinogenesis, Mutagenesis, Impairment of Fertility

Carcinogenesis

Long term studies in animals to evaluate carcinogenic potential have not been performed with XACIATO, or the active ingredient, clindamycin phosphate.

Mutagenesis

The genotoxic potential of clindamycin has been evaluated in a rat micronucleus test and an Ames Salmonella reversion test. Both tests were negative.

Impairment of Fertility

Fertility studies in rats treated vaginally with 2 mg/day clindamycin phosphate (0.1g/day XACIATO) or orally with 300 mg/kg/day (doses that are approximately equivalent to or 29-times the MRHD based on BSA comparisons, respectively) revealed no effects on fertility or mating ability.

14 CLINICAL STUDIES

The efficacy of XACIATO as a treatment of bacterial vaginosis (BV) in females 12 years of age and older was demonstrated in a randomized, double-blind, placebo-controlled clinical study (Trial 1, NCT04370548). A single dose of XACIATO (clindamycin phosphate vaginal gel, 2%) was compared to a single dose of placebo vaginal gel (hydroxyethylcellulose [HEC] Universal Placebo Gel) for the treatment of BV. Patients were evaluated at 3 timepoints: a Day 1 Screening/Randomization visit, a Day 7 to 14 Interim Assessment visit, and a Day 21 to 30 Test of Cure visit. The total study duration was up to approximately 1 month for each individual patient.

To be eligible, patients had to have a clinical diagnosis of BV defined as an off-white (milky or gray), thin, homogeneous discharge with minimal or absent pruritus and inflammation of the vulva and vagina, clue cells > 20% of the total epithelial cells on microscopic examination of the saline wet mount, vaginal secretion pH of > 4.5, and a fishy odor of the vaginal discharge with the addition of a drop of 10% KOH (i.e., a positive whiff test).

The 307 patients were randomized in a 2:1 ratio, with 204 in the XACIATO group and 103 in the placebo group. The modified Intent-To-Treat (mITT) Population excluded women with a positive test result for other concomitant vaginal or cervical infections at baseline, including a positive vaginal culture for Candida spp. or who had a baseline Nugent score of < 7.

Clinical Cure was defined as resolution of the abnormal vaginal discharge associated with BV, a negative 10% KOH whiff test, and clue cells < 20% of the total epithelial cells in the saline wet mount. Bacteriological Cure was defined as a Nugent score < 4. Therapeutic Cure was defined as the presence of both a Clinical Cure and Bacteriological Cure.

In the mITT population, a statistically significantly greater percentage of patients experienced Clinical Cure, Bacteriological Cure, and Therapeutic Cure at the Test of Cure (Day 21-30) visit in the XACIATO arm compared to placebo (Table 2). Statistically significant results for the endpoints were also achieved at the Interim Assessment visit (Day 7-14).

Table 2: Summary of Clinical Cure, Bacteriological Cure, and Therapeutic Cure (Modified Intent-to-Treat Population) in Trial 1
 | Interim Assessment visit (day 7-14) |  |  | Test of Cure visit (day 21-30)
Parameter | XACIATO (N = 122) n (%) | Placebo (N = 59) n (%) | Treatment Difference (%) [95% Confidence Interval] | XACIATO (N = 122) n (%) | Placebo (N = 59) n (%) | Treatment Difference (%) [95% Confidence Interval]
Clinical Cure | 93 (76.2) | 14 (23.7) | 52.5 (38.0, 67.0) | 86 (70.5) | 21 (35.6) | 34.9 (19.0, 50.8)
Bacteriological Cure | 50 (41.0) | 2 (3.4) | 37.6 (26.5, 48.7) | 53 (43.4) | 3 (5.1) | 38.4 (26.7, 50.1)
Therapeutic Cure | 43 (35.2) | 0 | 35.2 (25.5, 45.0) | 45 (36.9) | 3 (5.1) | 31.8 (20.3, 43.3)

All P-values for differences between treatment groups were <0.001 (from Cochran-Mantel-Haenszel test with strata of study site and race - African American or all other races).

The percentage of patients with Clinical Cure at the Test of Cure visit was also significantly higher in the XACIATO group compared to the placebo group among the subsets of patients defined by prior episodes of bacterial vaginosis (≤ 3 episodes and >3 episodes in the previous 12 months) at 71.3% (72/101) for XACIATO and 39.1% (18/46) placebo, and 70.0% (14/20) for XACIATO and 23.1% (3/13) placebo, respectively.

16 HOW SUPPLIED/STORAGE AND HANDLING

XACIATO vaginal gel, 2% is a clear, colorless, viscous gel supplied in a carton containing one 8-gram tube of vaginal gel and one vaginal applicator. One single-dose, user-filled disposable applicator delivers 5 g of gel containing 100 mg of clindamycin. NDC 78206-189-01.

Store at 68ºF to 77ºF (20ºC to 25ºC); excursions permitted to 59ºF to 86ºF (15ºC to 30ºC). [See USP Controlled Room temperature].

17 PATIENT COUNSELING INFORMATION

Advise the patient to read the FDA-approved patient labeling (Patient Information and Instructions for Use).

Vaginal Intercourse and Use with Vaginal Products

Instruct the patients not to engage in vaginal intercourse or use other vaginal products (such as tampons or douches) during treatment with XACIATO and for 3 days after using XACIATO.

Use with Polyurethane Condoms

Advise the patient that XACIATO may weaken polyurethane condoms. Therefore, use of polyurethane condoms concurrently or for 7 days following treatment with XACIATO is not recommended. During this time period polyurethane condoms may not be reliable for preventing pregnancy or for protecting against transmission of HIV and other sexually transmitted diseases. Latex or polyisoprene condoms should be used [see Warnings and Precautions (5.2)].

Vaginal Candida Infections

Inform the patient that vaginal yeast infections can occur following use of XACIATO and may require treatment with an antifungal drug [see Warnings and Precautions (5.3), Adverse Reactions (6.1)].

Distributed by: Organon LLC, a subsidiary of
ORGANON & Co.,
Jersey City, NJ 07302, USA

For patent information: www.organon.com/our-solutions/patent/

© 2025 Organon group of companies. All rights reserved.

uspi-og9423-gl-2512r001

PATIENT INFORMATION

XACIATO® (zah-she-AH-toe)

(clindamycin phosphate)

vaginal gel

Important Information: XACIATO is for intravaginal use only. Do not use in the eyes, mouth, or on your skin.

What is XACIATO?

- XACIATO vaginal gel is a prescription medicine used to treat bacterial vaginal infections in females 12 years of age and older.
- It is not known if XACIATO is safe and effective in children under 12 years of age.

Do not use XACIATO if you are:

- allergic to clindamycin or lincomycin.

Before using XACIATO, tell your healthcare provider about all of your medical conditions, including if you:

- have inflammatory bowel disease, including ulcerative colitis and Crohn’s disease.
- are pregnant or plan to become pregnant. It is not known if XACIATO will harm your unborn baby. Tell your healthcare provider if you become pregnant during treatment with XACIATO.
- are breastfeeding or plan to breastfeed. The amount of XACIATO which passes into your breast milk is low and is not expected to harm your baby. Talk with your healthcare provider about the best way to feed your baby while using XACIATO.

Tell your healthcare provider about all the medicines you take, including prescription and over-the-counter medicines, vitamins, and herbal supplements.

How should I use XACIATO?

- Use XACIATO exactly as your healthcare provider tells you to use it.
- Use 1 filled applicator of XACIATO in the vagina.
- Do not use any medicine from the tube or applicator more than 1 time. XACIATO is for 1 time (single-use) only.
- Do not use in the eyes, mouth, or on your skin.
- See the Instructions for Use at the end of this Patient Information leaflet for more information about how to fill the applicator and use XACIATO.

What should I avoid while using XACIATO?

After you insert XACIATO:

- Do not have vaginal sex or use vaginal products (such as tampons or douches) during treatment with XACIATO and for 3 days after using XACIATO.
- You should not use polyurethane condoms during treatment with XACIATO and for 7 days after using XACIATO. XACIATO may weaken polyurethane condoms and they may not work well for preventing pregnancy or protecting against Human Immunodeficiency Virus (HIV) and other sexually transmitted diseases (STDs). Latex or polyisoprene condoms should be used.

What are the possible side effects of XACIATO?

XACIATO may cause serious side effects, including diarrhea. One type of diarrhea is caused by an infection in your intestines called Clostridioides difficile-associated diarrhea (CDAD), which may range in severity from mild diarrhea to colitis that can lead to death. If you have diarrhea after you use XACIATO, call your healthcare provider.

The most common side effects of XACIATO include:

- Yeast infection in your vagina that may require treatment with an antifungal medicine.
- Vaginal discomfort including itching, burning, redness and dryness.

Tell your healthcare provider if you have any side effect that bothers you or that does not go away. These are not all the possible side effects of XACIATO. For more information, ask your healthcare provider or pharmacist.

Call your doctor for medical advice about side effects. You may report side effects to FDA at 1-800-FDA-1088.

How should I store XACIATO?

- Store XACIATO at room temperature between 68ºF and 77ºF (20ºC to 25ºC).

Keep XACIATO and all medicines out of the reach of children.

General information about the safe and effective use of XACIATO.

Medicines are sometimes prescribed for purposes other than those listed in a Patient Information leaflet. Do not use XACIATO for a condition for which it was not prescribed. Do not give XACIATO to other people, even if they have the same symptoms that you have. It may harm them. You can ask your pharmacist or healthcare provider for information about XACIATO that is written for health professionals.

What are the ingredients in XACIATO?

Active ingredient: clindamycin phosphate

Inactive ingredients: benzyl alcohol, citric acid monohydrate or citric acid anhydrous, poloxamer 407, purified water, sodium citrate dihydrate and xanthan gum.

Distributed by: Organon LLC, a subsidiary of
ORGANON & Co.,
Jersey City, NJ 07302, USA

For patent information: www.organon.com/our-solutions/patent/
© 2025 Organon group of companies. All rights reserved.
For more information, go to www.xaciato.com or call 1-844-674-3200
usppi-og9423-gl-2512r001

This Patient Information has been approved by the U.S. Food and Drug Administration. Revised: 12/2025

INSTRUCTIONS FOR USE

XACIATO® [zah-she-AH-toe]
(clindamycin phosphate vaginal gel 2%)

For vaginal use only. Do not use in the eyes or mouth, or on your skin.

Read these Instructions for Use before you use XACIATO® and each time you get a refill as there may be new information. This information does not take the place of talking to your healthcare provider about your medical condition or treatment.

Important Information

- Use XACIATO exactly as your healthcare provider tells you to use it.
- Use 1 filled applicator of XACIATO gel in your vagina.
- Do not use any medicine from the tube or applicator more than 1 time. The XACIATO gel is for 1 time (single-use) only.
- Do not have vaginal sex or use vaginal products (such as tampons or douches) during treatment with XACIATO gel and for 3 days after using XACIATO gel.
- Do not use polyurethane condoms during treatment with XACIATO gel and for 7 days after using XACIATO gel. XACIATO gel may weaken polyurethane condoms. Latex or polyisoprene condoms should be used.
- If you have questions or if your vaginal symptoms do not go away, contact your healthcare provider.

How do I store XACIATO?

- Store XACIATO gel at room temperature between 68ºF to 77ºF (20ºC to 25ºC).
- Do not store in the refrigerator or freezer.

Store XACIATO gel and all medicines out of the reach of children.

You will need the following included supplies (see Figure A):

- 1 single use tube containing the XACIATO gel
- 1 empty applicator, to fill and deliver the single dose of medicine.

Step 1. Remove the applicator and tube from the container box.

Step 2. Open the tube.

- Unscrew the cap from the tube (see Figure B1).

- Puncture the seal on the tube using the pointed tip on the cap by pushing the cap straight onto the tube (see Figure B2).
- Do not use the tube if it looks like it has been opened before.
- Do not use the tube if the seal is damaged or broken.

Step 3. Fill the applicator.

- While holding the applicator by the grip, screw the tip of the applicator (other end from the grip) onto the tube until it feels secure (see Figure C1).
- Leave plunger inside the applicator.

- Squeeze the tube from the bottom to push the XACIATO gel into the applicator (see Figure C2).

- The XACIATO gel will push the plunger up as the applicator fills (see Figure C3).

- Continue to fill the applicator until you see the black line on the plunger outside the applicator (see Figure C4).

- Unscrew the filled applicator from the tube.

Step 4. Prepare to insert the filled applicator.

- Lie on your back with your knees bent or in any comfortable position (see Figure D).

Step 5. Insert the filled applicator.

- Hold the filled applicator by the grip and gently insert the tip of the applicator into your vagina as far as it will comfortably go (see Figure E).

Step 6. Push the plunger.

- While holding the applicator in place, slowly push the plunger until it stops, to release all the XACIATO gel into your vagina (see Figure F).

Step 7. Remove the empty applicator from your vagina.

Step 8. Place the used applicator and tube in the container box and throw away (dispose of) in your household trash.

Distributed by: Organon LLC, a subsidiary of
ORGANON & Co.,
Jersey City, NJ 07302, USA

For patent information: www.organon.com/our-solutions/patent/
© 2025 Organon group of companies. All rights reserved.
For more information, go to www.xaciato.com or call 1-844-674-3200
usifu-og9423-gl-2512r001

This Instructions for Use has been approved by the U.S. Food and Drug Administration. Revised: 12/2025

PRINCIPAL DISPLAY PANEL - 8g Carton

NDC 78206-189-01

XACIATO®
(clindamycin phosphate) vaginal gel 2%

- 8g tube with one (1) 5g applicator
- Single-dose container
- Discard unused portion

FOR INTRAVAGINAL USE ONLY

Not for ophthalmic, dermal, or oral use

Keep out of reach of children

RECOMMENDED DOSAGE: See Prescribing Information
ADMINISTRATION: See Instructions for Use

Rx Only

Net Wt. 8 grams

Delivering 5 grams

PRINCIPAL DISPLAY PANEL - 8g Tube

NDC 78206-189-01

XACIATO®
(clindamycin phosphate) vaginal gel 2%

FOR INTRAVAGINAL USE ONLY

Not for ophthalmic, dermal, or oral use

Keep out of reach of children

Net Wt. 8 grams

Rx Only